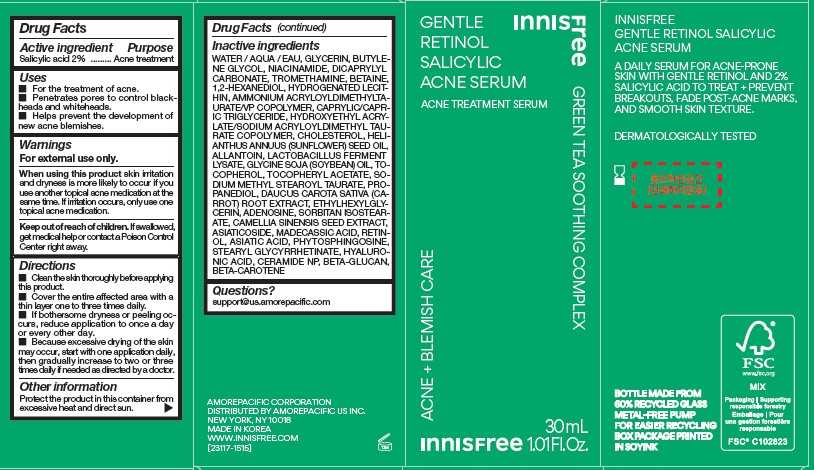 DRUG LABEL: innisfree Gentle Retinol Salicylic Acne Serum
NDC: 71220-088 | Form: GEL
Manufacturer: Innisfree Corporation
Category: otc | Type: HUMAN OTC DRUG LABEL
Date: 20250108

ACTIVE INGREDIENTS: SALICYLIC ACID 1 g/50 mL
INACTIVE INGREDIENTS: WATER; .ALPHA.-TOCOPHEROL, DL-; SODIUM METHYL STEAROYL TAURATE; SORBITAN ISOSTEARATE; ADENOSINE; ODETIGLUCAN; BUTYLENE GLYCOL; DICAPRYLYL CARBONATE; TROMETHAMINE; 1,2-HEXANEDIOL; ALLANTOIN; HYALURONIC ACID; GLYCERIN; NIACINAMIDE; BETAINE; CHOLESTEROL; HELIANTHUS ANNUUS (SUNFLOWER) SEED OIL; SOYBEAN OIL; PROPANEDIOL; MADECASSIC ACID; ASIATIC ACID; STEARYL GLYCYRRHETINATE; BETA CAROTENE; CAPRYLIC/CAPRIC TRIGLYCERIDE; RETINOL; ETHYLHEXYLGLYCERIN; CAMELLIA SINENSIS SEED; ASIATICOSIDE; CARROT; .ALPHA.-TOCOPHEROL ACETATE; CERAMIDE NP; HYDROXYETHYL ACRYLATE/SODIUM ACRYLOYLDIMETHYL TAURATE COPOLYMER (45000 MPA.S AT 1%); PHYTOSPHINGOSINE

innisfree Gentle Retinol Salicylic Acne Serum

Drug Facts

ACTIVE INGREDIENTS

Salicylic acid 2%

Purpose

Acne treatment

Uses

- For the treatment of acne.
- Penetrates pores to control blackheads and whiteheads.
- Helps prevent the development of new acne blemishes.

Warnings

For external use only

When using this product skin irritation and dryness is more likely to occur if you use another topical acne medication at the same time. If irritation occurs, only use one topical acne medication .

Keep out of reach of children. If swallowed, get medical help or contact a Poison Control Center right away.

Directions

■ Clean the skin thoroughly before applying this product.
■ Cover the entire affected area with a thin layer one to three times daily.
■ If bothersome dryness or peeling occurs, reduce application to once a day
or every other day.
■ Because excessive drying of the skin may occur, start with one application daily, then gradually increase to two or three times daily if needed as directed by a doctor.

Other information

Protect the product in this container from excessive heat and direct sun

Inactive ingredients

WATER / AQUA / EAU, GLYCERIN, BUTYLENE GLYCOL, NIACINAMIDE, DICAPRYLYL CARBONATE, TROMETHAMINE, BETAINE,
1,2-HEXANEDIOL, HYDROGENATED LECITHIN, AMMONIUM ACRYLOYLDIMETHYLTAURATE/VP COPOLYMER, CAPRYLIC/CAPRIC TRIGLYCERIDE, HYDROXYETHYL ACRYLATE/SODIUM ACRYLOYLDIMETHYL TAURATE
COPOLYMER, CHOLESTEROL, HELIANTHUS ANNUUS (SUNFLOWER) SEED OIL, ALLANTOIN, LACTOBACILLUS FERMENT LYSATE, GLYCINE SOJA (SOYBEAN) OIL, TOCOPHEROL, TOCOPHERYL ACETATE, SODIUM
METHYL STEAROYL TAURATE, PROPANEDIOL, DAUCUS CAROTA SATIVA (CARROT) ROOT EXTRACT, ETHYLHEXYLGLYCERIN, ADENOSINE, SORBITAN ISOSTEARATE, CAMELLIA SINENSIS SEED EXTRACT, ASIATICOSIDE, MADECASSIC ACID, RETINOL, ASIATIC ACID, PHYTOSPHINGOSINE, STEARYL GLYCYRRHETINATE, HYALURONIC ACID, CERAMIDE NP, BETA-GLUCAN, BETA-CAROTENE

Questions?

support@us.amorepacific.com

Innisfree GENTLE RETINOL SALICYLIC ACNE SERUM

Innisfree

GENTLE RETINOL SALICYLIC ACNE SERUM
ACNE TREATMENT SERUM

GREEN TEA SOOTHING COMPLEX
ACNE + BLEMISH CARE

30 mL
1.01 Fl. Oz.